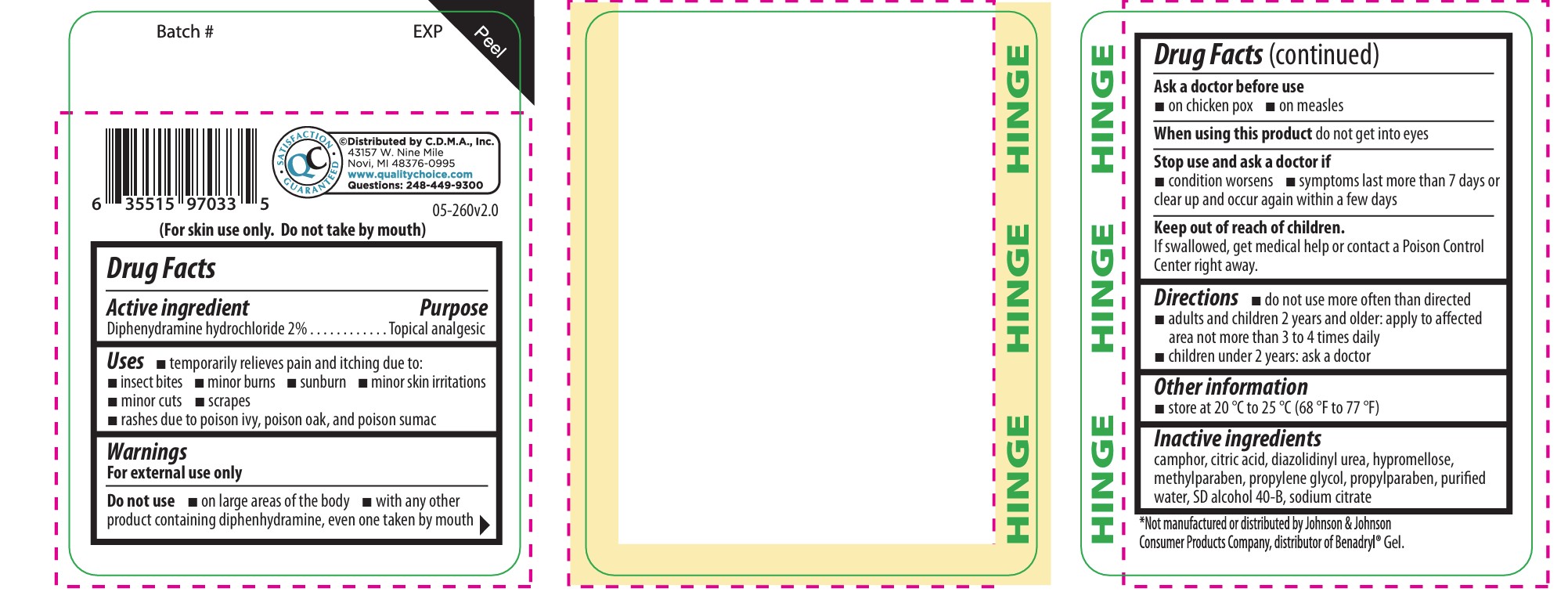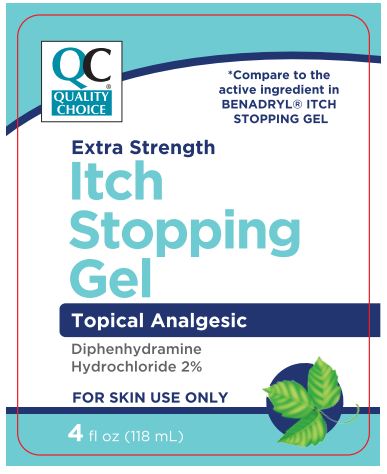 DRUG LABEL: Itch Stopping
NDC: 63868-260 | Form: GEL
Manufacturer: Chain Drug Marketing Association
Category: otc | Type: HUMAN OTC DRUG LABEL
Date: 20251112

ACTIVE INGREDIENTS: DIPHENHYDRAMINE HYDROCHLORIDE 2 g/100 g
INACTIVE INGREDIENTS: DIAZOLIDINYL UREA; METHYLPARABEN; TRISODIUM CITRATE DIHYDRATE; ALCOHOL; WATER; PROPYLENE GLYCOL; ANHYDROUS CITRIC ACID; HYPROMELLOSE 2910 (4000 MPA.S); CAMPHOR (SYNTHETIC); PROPYLPARABEN

Quality Choice Extra Strength Itch Stopping Gel

ACTIVE INGREDIENT

Diphenhydramine hydrochloride 2%..

INDICATIONS AND USAGE

itching due to:

insect bites

minor burns

sunburn

minor skin irritations

minor cuts

scrapes

rashes due to poison ivy, poison oak, and poison sumac

WARNINGS

For external use only

Do Not Use

on large areas of the body

with any other product containing diphenhydramine, even one taken by mouth

Ask Doctor Before Use

On chiken Pox

On Measles

When Using This Product

do not get into eyes

Stop Use and ask Doctor if

condition worsens

symptoms last more than 7 days or clear up and occur again within a few days

Keep out of reach of children

If swallowed, get medical help or contact a Poison Control Center right away.

PURPOSE

Anti itch

Topical analgesic

Other

store at 20 °C to 25 °C (68 °F to 77 °F)

INACTIVE INGREDIENT

camphor, citric acid, diazolidinyl urea, hypromellose, methylparaben, propylene glycol, propylparaben, purified water,
SD alcohol 40-B, sodium citrate

do not use more often than directed

adults and children 2 years and older: apply to affected area not more than 3 to 4 times daily

children under 2 years: ask a doctor

RECENT MAJOR CHANGES

Dosage & Administration Section

Added - do not use more often than directed

PACKAGE LABEL

Quality Choice QC

Compare to the active ingredient in Benadryl Gel

Extra strength Itch Relief Gel

Topical Analgesic

Diphenhydramine HCL 2%

For skin use only